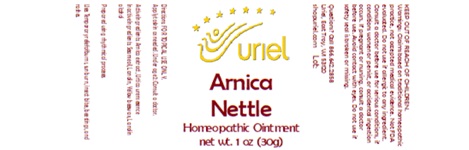 DRUG LABEL: Arnica Nettle
NDC: 48951-1400 | Form: OINTMENT
Manufacturer: Uriel Pharmacy, Inc
Category: homeopathic | Type: HUMAN OTC DRUG LABEL
Date: 20251208

ACTIVE INGREDIENTS: URTICA URENS 1 [hp_X]/1 g; ARNICA MONTANA FLOWER 1 [hp_X]/1 g
INACTIVE INGREDIENTS: LANOLIN; BEESWAX; LANOLIN ALCOHOL; SUNFLOWER OIL

Arnica Nettle

INDICATIONS AND USAGE

Directions: FOR TOPICAL USE ONLY.

DOSAGE AND ADMINISTRATION

Apply to skin as needed. Under age 2: Consult a doctor.

Active Ingredients: Arnica extract, Urtica urens essence

INACTIVE INGREDIENT

Inactive Ingredients: Sunflower seed oil, Lanolin, Yellow beeswax, Lanolin alcohol

Prepared using rhythmical processes.

PURPOSE

Uses: Temporary relief of burns, sunburn, insect bites, bee stings, and rashes.

KEEP OUT OF REACH OF CHILDREN.

WARNINGS

Warnings: Claims based on traditional homeopathic practice, not accepted medical evidence. Not FDA evaluated. Do not use if allergic to any ingredient. Consult a doctor before use for serious conditions, if conditions worsen or persist, or accidental ingestion occurs. If pregnant or nursing, consult a doctor before use. Avoid contact with eyes. Do not use if safety seal is broken or missing.

Questions? Call 866.642.2858
Uriel, East Troy, WI 53120
shopuriel.com Lot: